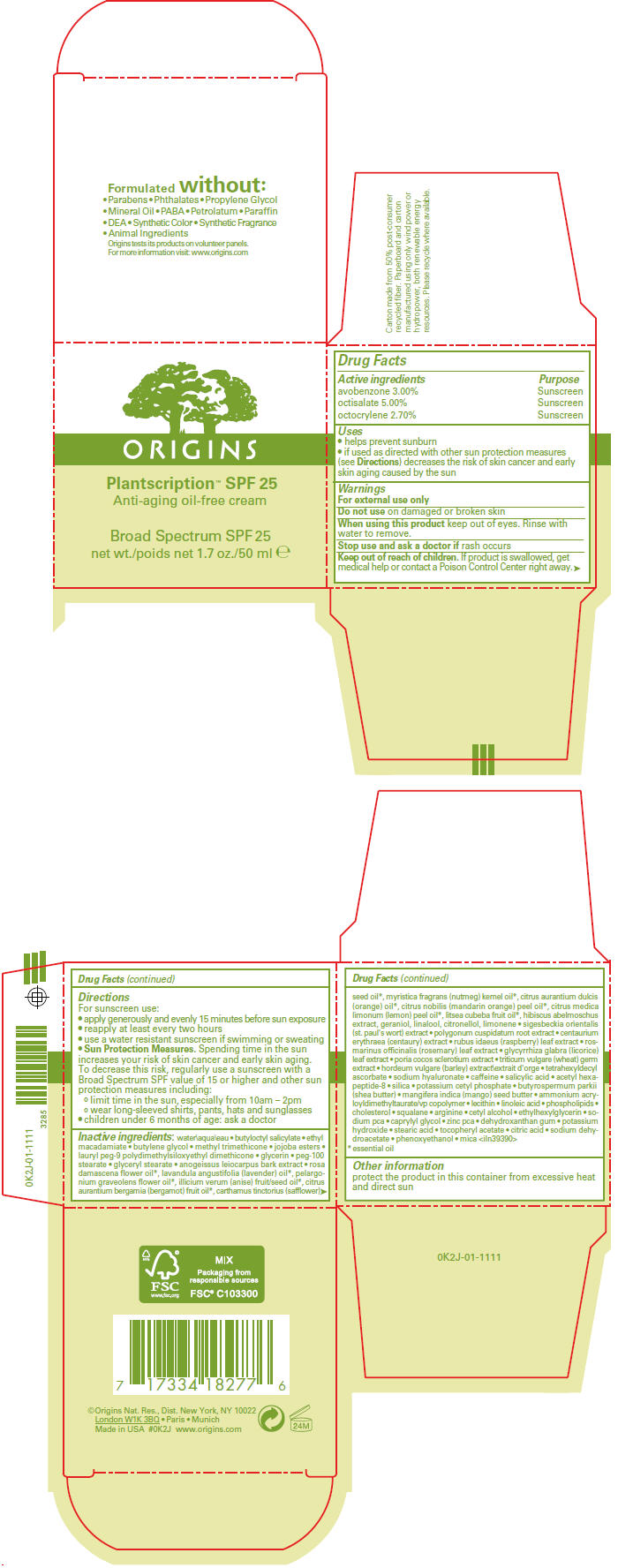 DRUG LABEL: PLANTSCRIPTION ANTI AGING OIL FREE BROAD SPECTRUM SPF 25
NDC: 59427-007 | Form: CREAM
Manufacturer: ORIGINS NATURAL RESOURCES INC.
Category: otc | Type: HUMAN OTC DRUG LABEL
Date: 20130325

ACTIVE INGREDIENTS: AVOBENZONE 0.0303 g/1 mL; OCTISALATE 0.0505 g/1 mL; OCTOCRYLENE 0.02727 g/1 mL
INACTIVE INGREDIENTS: water; butyloctyl salicylate; ethyl macadamiate; butylene glycol; methyl trimethicone; lauryl peg-9 polydimethylsiloxyethyl dimethicone; glycerin; peg-100 stearate; glyceryl monostearate; anogeissus leiocarpus bark; rosa damascena flower oil; lavender oil; pelargonium graveolens flower oil; star anise oil; bergamot oil; safflower oil; nutmeg oil; orange oil; mandarin oil; lemon oil; litsea oil; geraniol; linalool, (+/-)-; .beta.-citronellol, (r)-; polygonum cuspidatum root; centaurium erythraea; rubus idaeus leaf; rosemary; glycyrrhiza glabra leaf; wheat germ; tetrahexyldecyl ascorbate; hyaluronate sodium; caffeine; salicylic acid; acetyl hexapeptide-8; silicon dioxide; potassium cetyl phosphate; shea butter; mangifera indica seed butter; ammonium acryloyldimethyltaurate/vp copolymer; linoleic acid; cholesterol; squalane; arginine; cetyl alcohol; ethylhexylglycerin; sodium pyrrolidone carboxylate; caprylyl glycol; zinc pidolate; potassium hydroxide; stearic acid; .alpha.-tocopherol acetate; citric acid monohydrate; sodium dehydroacetate; phenoxyethanol; mica

PLANTSCRIPTION™ ANTI AGING OIL FREE CREAM BROAD SPECTRUM SPF 25

Drug Facts

ACTIVE INGREDIENT

Active ingredients | Purpose
avobenzone 3.00% | Sunscreen
octisalate 5.00% | Sunscreen
octocrylene 2.70% | Sunscreen

Uses

- helps prevent sunburn
- if used as directed with other sun protection measures (see Directions) decreases the risk of skin cancer and early skin aging caused by the sun

Warnings

For external use only

Do not use on damaged or broken skin

When using this product keep out of eyes. Rinse with water to remove.

Stop use and ask a doctor if rash occurs

Keep out of reach of children. If product is swallowed, get medical help or contact a Poison Control Center right away.

Directions

For sunscreen use:

- apply generously and evenly 15 minutes before sun exposure
- reapply at least every two hours
- use a water resistant sunscreen if swimming or sweating
- Sun Protection Measures. Spending time in the sun increases your risk of skin cancer and early skin aging. To decrease this risk, regularly use a sunscreen with a Broad Spectrum SPF value of 15 or higher and other sun protection measures including:
  - limit time in the sun, especially from 10am – 2pm
  - wear long-sleeved shirts, pants, hats and sunglasses
- children under 6 months of age: ask a doctor

Inactive ingredients

water\aqua\eau • butyloctyl salicylate • ethyl macadamiate • butylene glycol • methyl trimethicone • jojoba esters • lauryl peg-9 polydimethylsiloxyethyl dimethicone • glycerin • peg-100 stearate • glyceryl stearate • anogeissus leiocarpus bark extract • rosa damascena flower oil [essential oil] , lavandula angustifolia (lavender) oil, pelargonium graveolens flower oil, illicium verum (anise) fruit/seed oil, citrus aurantium bergamia (bergamot) fruit oil, carthamus tinctorius (safflower) seed oil, myristica fragrans (nutmeg) kernel oil, citrus aurantium dulcis (orange) oil, citrus nobilis (mandarin orange) peel oil, citrus medica limonum (lemon) peel oil, litsea cubeba fruit oil, hibiscus abelmoschus extract, geraniol, linalool, citronellol, limonene • sigesbeckia orientalis (st. paul's wort) extract • polygonum cuspidatum root extract • centaurium erythraea (centaury) extract • rubus idaeus (raspberry) leaf extract • rosmarinus officinalis (rosemary) leaf extract • glycyrrhiza glabra (licorice) leaf extract • poria cocos sclerotium extract • triticum vulgare (wheat) germ extract • hordeum vulgare (barley) extract\extrait d'orge • tetrahexyldecyl ascorbate • sodium hyaluronate • caffeine • salicylic acid • acetyl hexapeptide-8 • silica • potassium cetyl phosphate • butyrospermum parkii (shea butter) • mangifera indica (mango) seed butter • ammonium acryloyldimethyltaurate/vp copolymer • lecithin • linoleic acid • phospholipids • cholesterol • squalane • arginine • cetyl alcohol • ethylhexylglycerin • sodium pca • caprylyl glycol • zinc pca • dehydroxanthan gum • potassium hydroxide • stearic acid • tocopheryl acetate • citric acid • sodium dehydroacetate • phenoxyethanol • mica <iln39390>

Other information

protect the product in this container from excessive heat and direct sun

PRINCIPAL DISPLAY PANEL - 50 mL Jar Carton

ORIGINS

Plantscription™ SPF 25
Anti-aging oil-free cream

Broad Spectrum SPF 25
net wt./poids net 1.7 oz./50 ml e